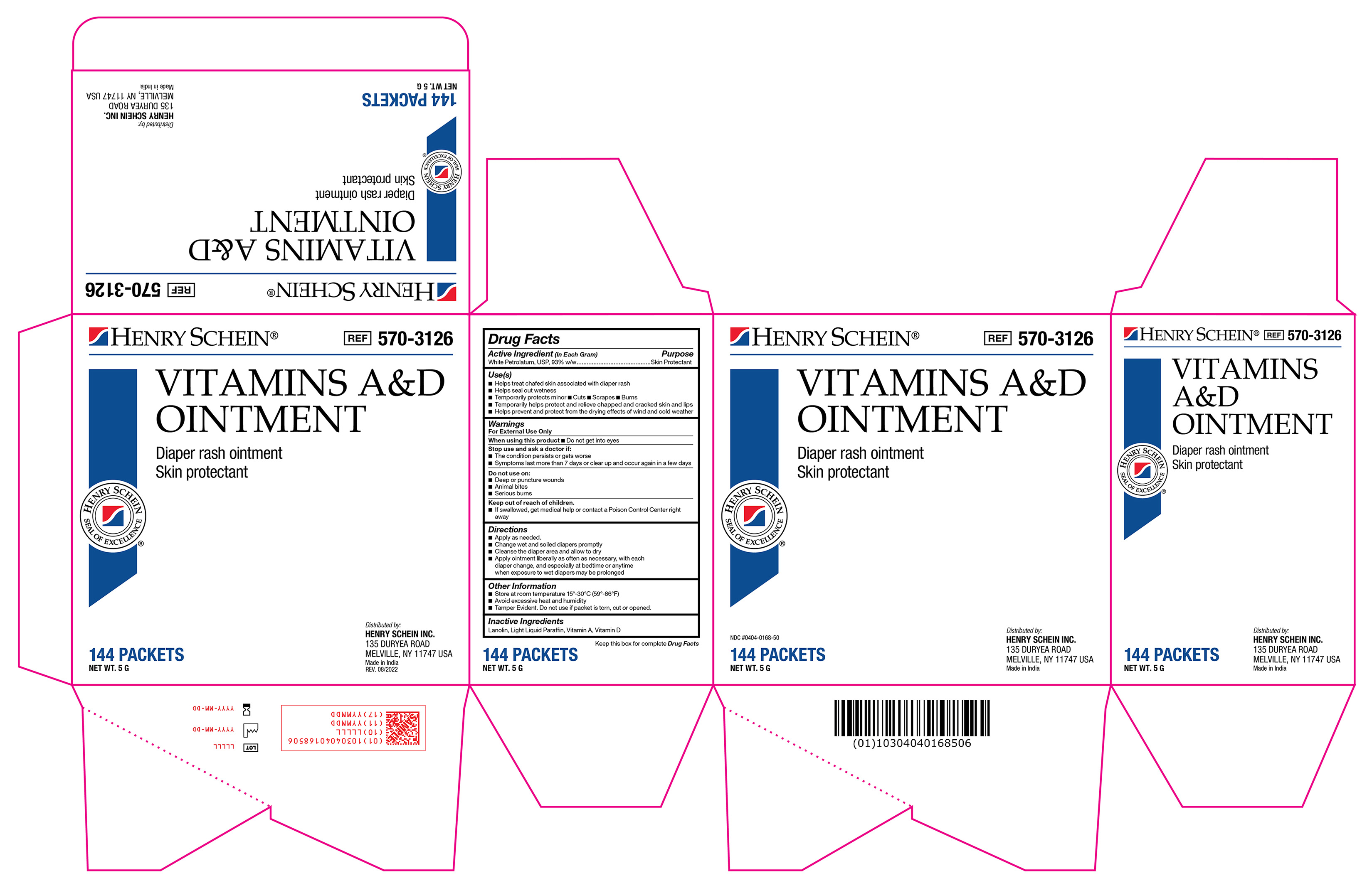 DRUG LABEL: Vitamin A D
NDC: 0404-0168 | Form: OINTMENT
Manufacturer: Henry Schein
Category: otc | Type: HUMAN OTC DRUG LABEL
Date: 20251125

ACTIVE INGREDIENTS: WHITE PETROLATUM 93 g/100 g
INACTIVE INGREDIENTS: LANOLIN; LIGHT MINERAL OIL; VITAMIN D; VITAMIN A

570-3126 Vitamins A&D Ointment NDC 0404-0168

Active Ingredient

White Petrolatum 93% w/w

Purpose

Skin Protectant

Use(s)

• Helps treat chafed skin associated with diaper rash

• Helps seal out wetness

• Temporarily protects minor • Cuts • Scrapes • Burns

• Temporarily helps protect and relieve chapped and cracked skin and lips

• Helps prevent and protect from the drying effects of wind and cold weather

Warnings

For External Use Only

When using this product

Do not get into eyes

Stop use and ask a doctor if

• The condition persists or gets worse

• Symptoms last more than 7 days or clear up and occur again in a few days

Do not use on

• Deep or puncture wounds

• Animal bites

• Serious burns

Keep out of reach of children

If swallowed, get medical help or contact a Poison Control Center (1-800-222-1222) right away.

Directions

• Apply as needed

• Change wet and soiled diapers promptly

• Cleanse the diaper area and allow to dry

• Apply ointment liberally as often as necessary, with each diaper change, and especially at bedtime or anytime when exposure to wet diapers may be prolonged.

Other Information

• Store at room temperature 15º-30ºC (59º-86ºF)

• Avoid excessive heat and humidity

• Tamper evident. Do not use if packet is torn, cut, or opened.

Inactive Ingredients

Lanolin, Light Mineral Oil, Vitamin A, Vitamin D

Label

Vitamins A&D Ointment